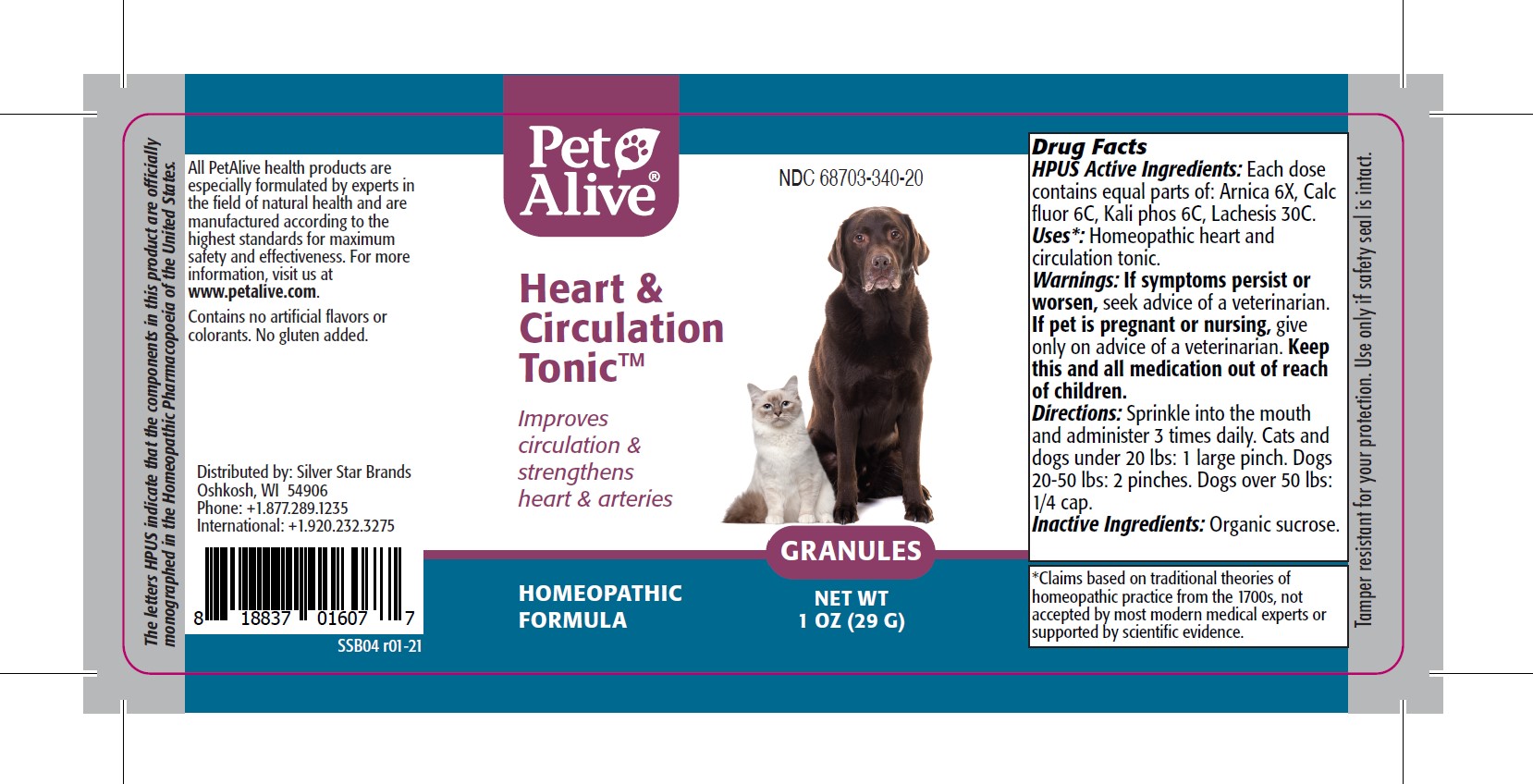 DRUG LABEL: PetAlive Heart and Circulation Tonic
NDC: 68703-340 | Form: GRANULE
Manufacturer: SILVER STAR BRANDS
Category: homeopathic | Type: OTC ANIMAL DRUG LABEL
Date: 20251216

ACTIVE INGREDIENTS: ARNICA MONTANA 6 [hp_X]/50 mg; CALCIUM FLUORIDE 6 [hp_C]/50 mg; POTASSIUM PHOSPHATE, DIBASIC 6 [hp_C]/50 mg; LACHESIS MUTA VENOM 30 [hp_C]/50 mg
INACTIVE INGREDIENTS: SUCROSE

PetAlive Heart and Circulation Tonic

PURPOSE

Improves circulation and strengthens heart and arteries

HPUS Active Ingredients:

Arnica 6X
Calc fluor 6C
Kali phos 6C
Lachesis 30C

INDICATIONS AND USAGE

Uses: Homeopathic heart and circulation tonic.

WARNINGS

Warnings: If symptoms persist or worsen, seek advice of a veterinarian.

PREGNANCY OR BREAST FEEDING

If pet is pregnant or nursing, give only on advice of a veterinarian.

KEEP OUT OF REACH OF CHILDREN

Keep this and all medication out of reach of children.

DOSAGE AND ADMINISTRATION

Directions: Sprinkle into the mouth and administer 3 times daily. Cats and dogs under 20 lbs: 1 large pinch. Dogs 20-50 lbs: 2 pinches. Dogs over 50 lbs: 1/4 сар.

Inactive Ingredients: Organic sucrose.

INFORMATION FOR OWNERS/CAREGIVERS

The letters HPUS indicate that the components in this product are officially monographed in the Homeopathic Pharmacopoeia of the United States.

All PetAlive health products are especially formulated by experts in the field of natural health and are manufactured according to the highest standards for maximum safety and effectiveness. For more information, visit us at www.petalive.com.

Contains no artificial flavors or colorants. No gluten added.

Distributed by: Silver Star Brands
Oshkosh, WI 54906
Phone: +1.877.289.1235
International: +1.920.232.3275

STORAGE AND HANDLING

Tamper resistant for your protection. Use only if safety seal is intact.